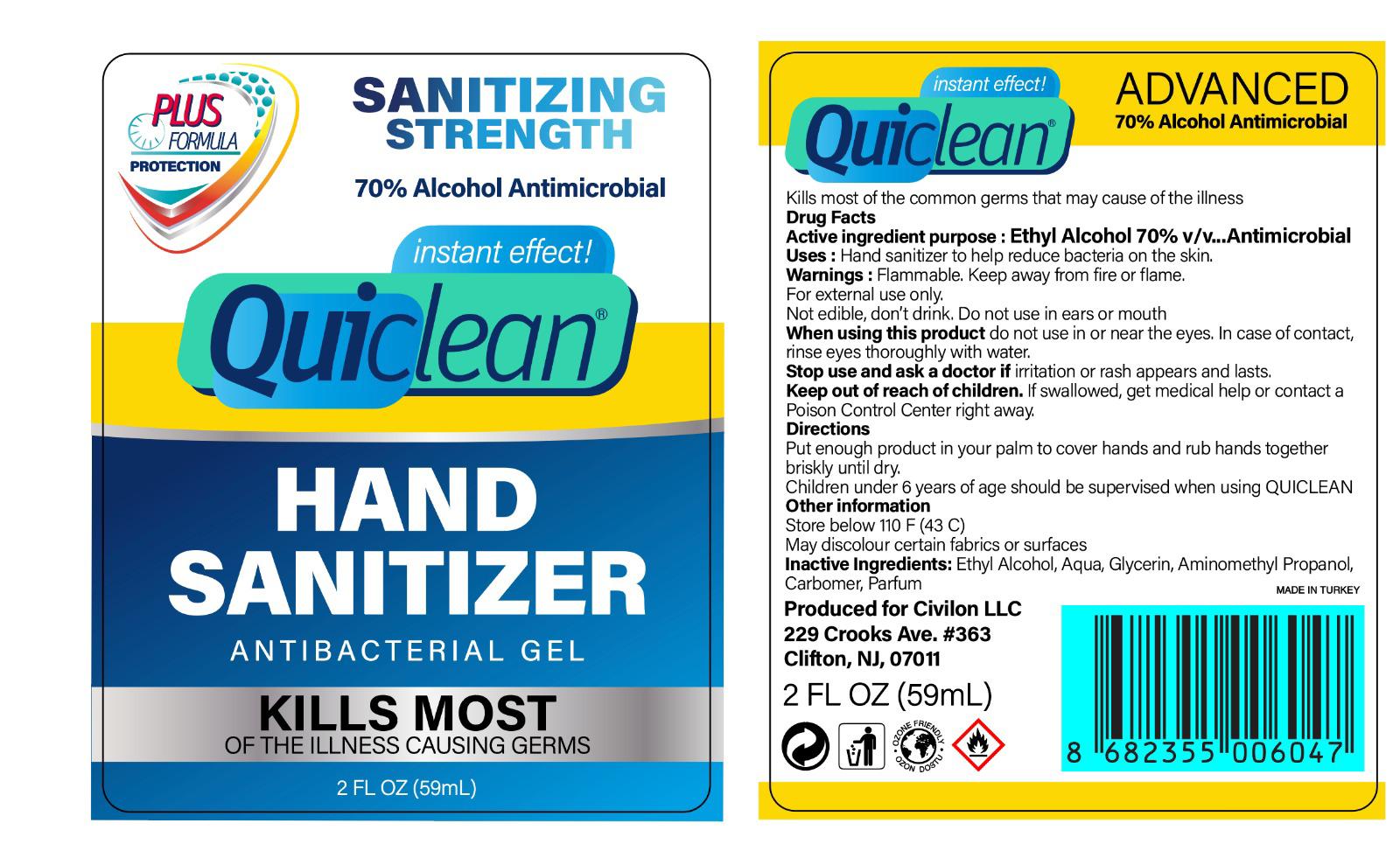 DRUG LABEL: Quiclean
NDC: 77222-222 | Form: GEL
Manufacturer: SIRIUS KOZMETIK SANAYI VE TICARET ANONIM SIRKETI
Category: otc | Type: HUMAN OTC DRUG LABEL
Date: 20200709

ACTIVE INGREDIENTS: ALCOHOL 70 mL/100 mL
INACTIVE INGREDIENTS: BITTER ORANGE OIL; CARBOMER HOMOPOLYMER, UNSPECIFIED TYPE; GLYCERIN; AMINOMETHYLPROPANOL; WATER

SIRIUS-GEL

Active Ingredient(s)

Alcohol 70% v/v

Purpose

Antimicrobial

Use

Hand Sanitizer to help reduce bacteria that potentially can cause disease. For use when soap and water are not available.

Warnings

For external use only. Flammable. Keep away from heat or flame.

Not edible, don't drink. Do not use in ears or mouth.

When using this product keep out of eyes, ears, and mouth. In case of contact with eyes, rinse eyes thoroughly with water.
Stop use and ask a doctor if irritation or rash occurs. These may be signs of a serious condition.
Keep out of reach of children. If swallowed, get medical help or contact a Poison Control Center right away.

Stop use and ask a doctor if irritation or rash occurs. These may be signs of a serious condition.

Keep out of reach of children. If swallowed, get medical help or contact a Poison Control Center right away.

Directions

Put enough product in your palm to cover hands and rub hands together briskly until dry.

Children under 6 years age should be supervised when using QUICLEAN.

Other information

- Store below 110 F (43C)
- May discolor certain fabrics or surfaces.

Inactive ingredients

Water (Aqua), Glycerin, Aminomethyl Propanol, Carbomer, Perfume (Bitter Orange oil)

Package Label - Principal Display Panel

59 mL NDC: 77222-222-01